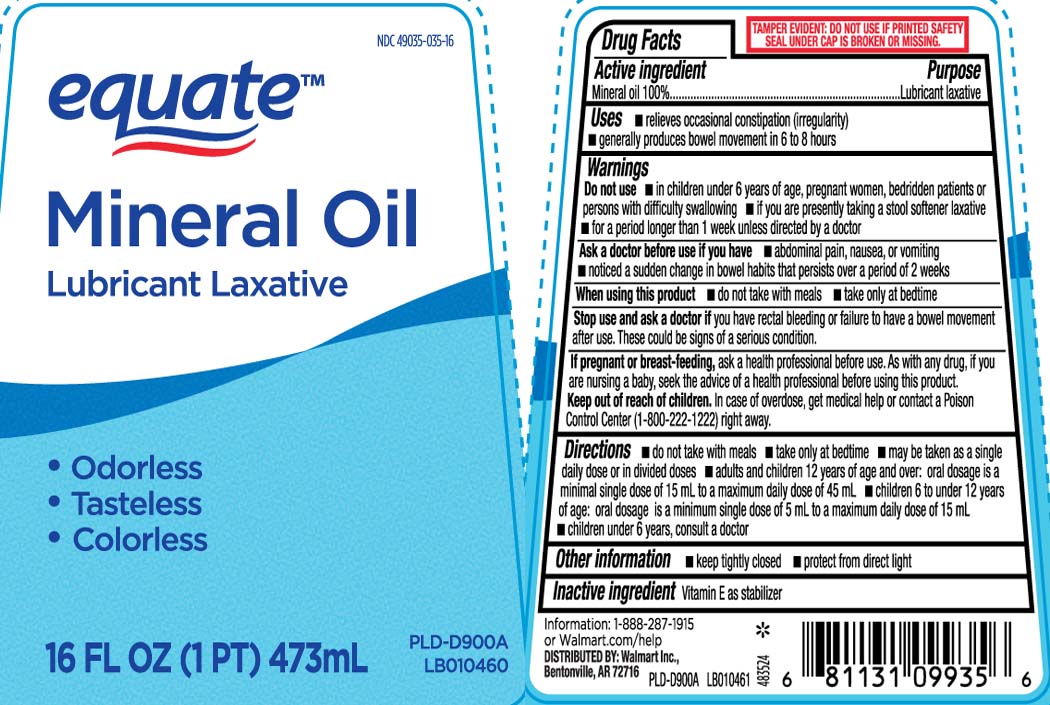 DRUG LABEL: Mineral oil
NDC: 49035-035 | Form: OIL
Manufacturer: EQUATE (Wal-Mart Stores, Inc.) (see also WAL-MART INC)
Category: otc | Type: HUMAN OTC DRUG LABEL
Date: 20250715

ACTIVE INGREDIENTS: MINERAL OIL 100 mg/100 mL
INACTIVE INGREDIENTS: TOCOPHEROL

Drug Facts

Active ingredient

Mineral oil 100%

Purpose

Lubricant laxative

Uses

- relieves occasional constipation (irregularity)
- generally produces bowel movement in 6 to 8 hours

Warnings

Do not use

- in children under 12 years of age, pregnant women, bedridden patients or aged, or if you have difficulty swallowing
- if you are presently taking a stool softener laxative
- for a period longer than 1 week unless directed by a doctor

Ask a doctor before use if you have

- abdominal pain, nausea, or vomiting
- noticed a sudden change in bowel habits that persists over a period of 2 weeks

When using this product

- do not take with meals
- take only at bedtime

Stop use and ask a doctor if

you have rectal bleeding or failure to have a bowel movement after use. These could be signs of a serious condition.

If pregnant or breast-feeding,

ask a health professional before use. As with any drug, if you are nursing a baby, seek the advice of a health professional before using this product.

Keep out of reach of children.

In case of overdose, get medical help or contact a Poison Control Center (1-800-222-1222) right away.

Directions

- do not take with meals
- take only at bedtime
- may be taken as a single daily dose or in divided doses
- adults and children 12 years of age and over: oral dosage is a minimal single dose of 15 mL to a maximum daily dose of 45 mL
- children 6 to under 12 years of age: oral dosage is a minimum single dose of 5 mL to a maximum daily dose of 15 mL
- Children under 6 years, consult a doctor

Other information

- keep tightly closes
- protect from direct light

Inactive ingredients

Vitamin E as stabilizer

Questions or comments?

Call 1-888-287-1915

Principal Display Panel

Mineral Oil

Lubricant Laxative

- Odorless
- Tasteless
- Colorless

FL OZ (mL)

TAMPER EVIDENT: DO NOT USE IF PRINTED SAFETY SEAL UNDER CAP IS BROKEN OR MISSING.

Distributed by Wal-Mart Inc.,

Bentonville, AR 72716

Package Label

EQUATE Mineral Oil